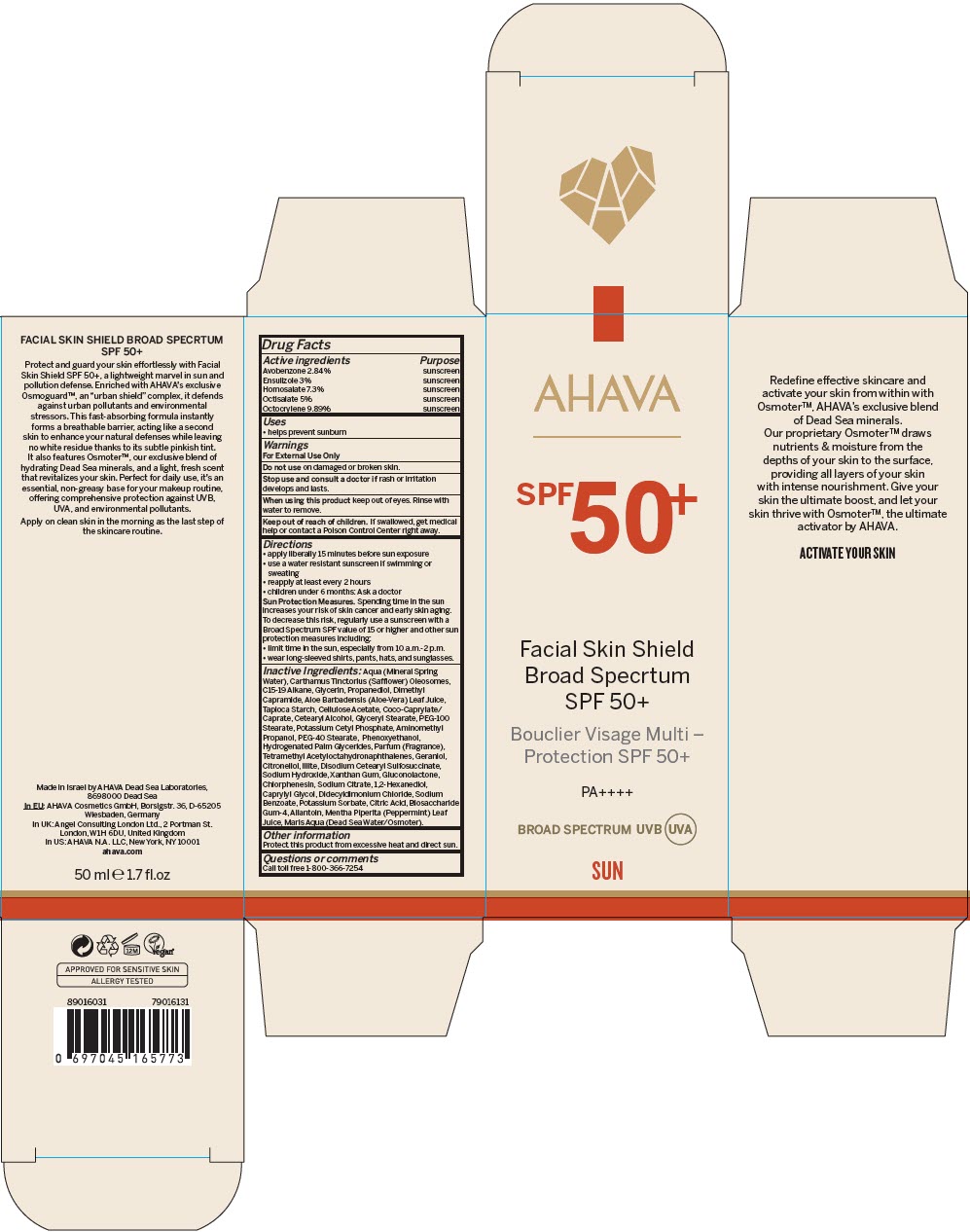 DRUG LABEL: Facial Skin Shield Broad Spectrum SPF50 Plus
NDC: 60289-302 | Form: CREAM
Manufacturer: AHAVA - Dead Sea Laboratories Ltd
Category: otc | Type: HUMAN OTC DRUG LABEL
Date: 20241120

ACTIVE INGREDIENTS: AVOBENZONE 0.0284 g/1 mL; ENSULIZOLE 0.03 g/1 mL; HOMOSALATE 0.073 g/1 mL; OCTISALATE 0.05 g/1 mL; OCTOCRYLENE 0.0989 g/1 mL
INACTIVE INGREDIENTS: WATER; CARTHAMUS TINCTORIUS SEED OLEOSOMES; C15-19 ALKANE; GLYCERIN; PROPANEDIOL; DIMETHYL CAPRAMIDE; ALOE VERA LEAF; STARCH, TAPIOCA; CELLULOSE ACETATE; COCOYL CAPRYLOCAPRATE; CETOSTEARYL ALCOHOL; GLYCERYL MONOSTEARATE; PEG-100 STEARATE; POTASSIUM CETYL PHOSPHATE; AMINOMETHYLPROPANOL; PEG-40 MONOSTEARATE; PHENOXYETHANOL; HYDROGENATED PALM GLYCERIDES; TETRAMETHYL ACETYLOCTAHYDRONAPHTHALENES; GERANIOL; .BETA.-CITRONELLOL, (R)-; LEDIKITE; SODIUM HYDROXIDE; XANTHAN GUM; GLUCONOLACTONE; CHLORPHENESIN; SODIUM CITRATE, UNSPECIFIED FORM; 1,2-HEXANEDIOL; CAPRYLYL GLYCOL; DIDECYLDIMONIUM CHLORIDE; SODIUM BENZOATE; POTASSIUM SORBATE; CITRIC ACID MONOHYDRATE; BIOSACCHARIDE GUM-4; ALLANTOIN; MENTHA PIPERITA LEAF

Facial Skin Shield Broad Spectrum SPF50+

Drug Facts

ACTIVE INGREDIENT

Active ingredients | Purpose
Avobenzone 2.84% | sunscreen
Ensulizole 3% | sunscreen
Homosalate 7.3% | sunscreen
Octisalate 5% | sunscreen
Octocrylene 9.89% | sunscreen

Uses

- helps prevent sunburn

Warnings

For External Use Only

Do not use on damaged or broken skin.

Stop use and consult a doctor if rash or irritation develops and lasts.

When using this product keep out of eyes. Rinse with water to remove.

Keep out of reach of children. If swallowed, get medical help or contact a Poison Control Center right away.

Directions

- apply liberally 15 minutes before sun exposure
- use a water resistant sunscreen if swimming or sweating
- reapply at least every 2 hours
- children under 6 months: Ask a doctor

Sun Protection Measures

Spending time in the sun increases your risk of skin cancer and early skin aging. To decrease this risk, regularly use a sunscreen with a Broad Spectrum SPF value of 15 or higher and other sun protection measures including:

- limit time in the sun, especially from 10 a.m.-2 p.m.
- wear long-sleeved shirts, pants, hats, and sunglasses.

Inactive Ingredients

Aqua (Mineral Spring Water), Carthamus Tinctorius (Safflower) Oleosomes, C15-19 Alkane, Glycerin, Propanediol, Dimethyl Capramide, Aloe Barbadensis (Aloe-Vera) Leaf Juice, Tapioca Starch, Cellulose Acetate, Coco-Caprylate/ Caprate, Cetearyl Alcohol, Glyceryl Stearate, PEG-100 Stearate, Potassium Cetyl Phosphate, Aminomethyl Propanol, PEG-40 Stearate, Phenoxyethanol, Hydrogenated Palm Glycerides, Parfum (Fragrance), Tetramethyl Acetyloctahydronaphthalenes, Geraniol, Citronellol, Illite, Disodium Cetearyl Sulfosuccinate, Sodium Hydroxide, Xanthan Gum, Gluconolactone, Chlorphenesin, Sodium Citrate, 1,2-Hexanediol, Caprylyl Glycol, Didecyldimonium Chloride, Sodium Benzoate, Potassium Sorbate, Citric Acid, Biosaccharide Gum-4, Allantoin, Mentha Piperita (Peppermint) Leaf Juice, Maris Aqua (Dead Sea Water/Osmoter).

Other information

Protect this product from excessive heat and direct sun.

Questions or comments

Call toll free 1-800-366-7254

PRINCIPAL DISPLAY PANEL - 50 ml Bottle Carton

AHAVA

SPF 50^+

Facial Skin Shield
Broad Specrtum
SPF 50+

PA++++

BROAD SPECTRUM UVB UVA

SUN